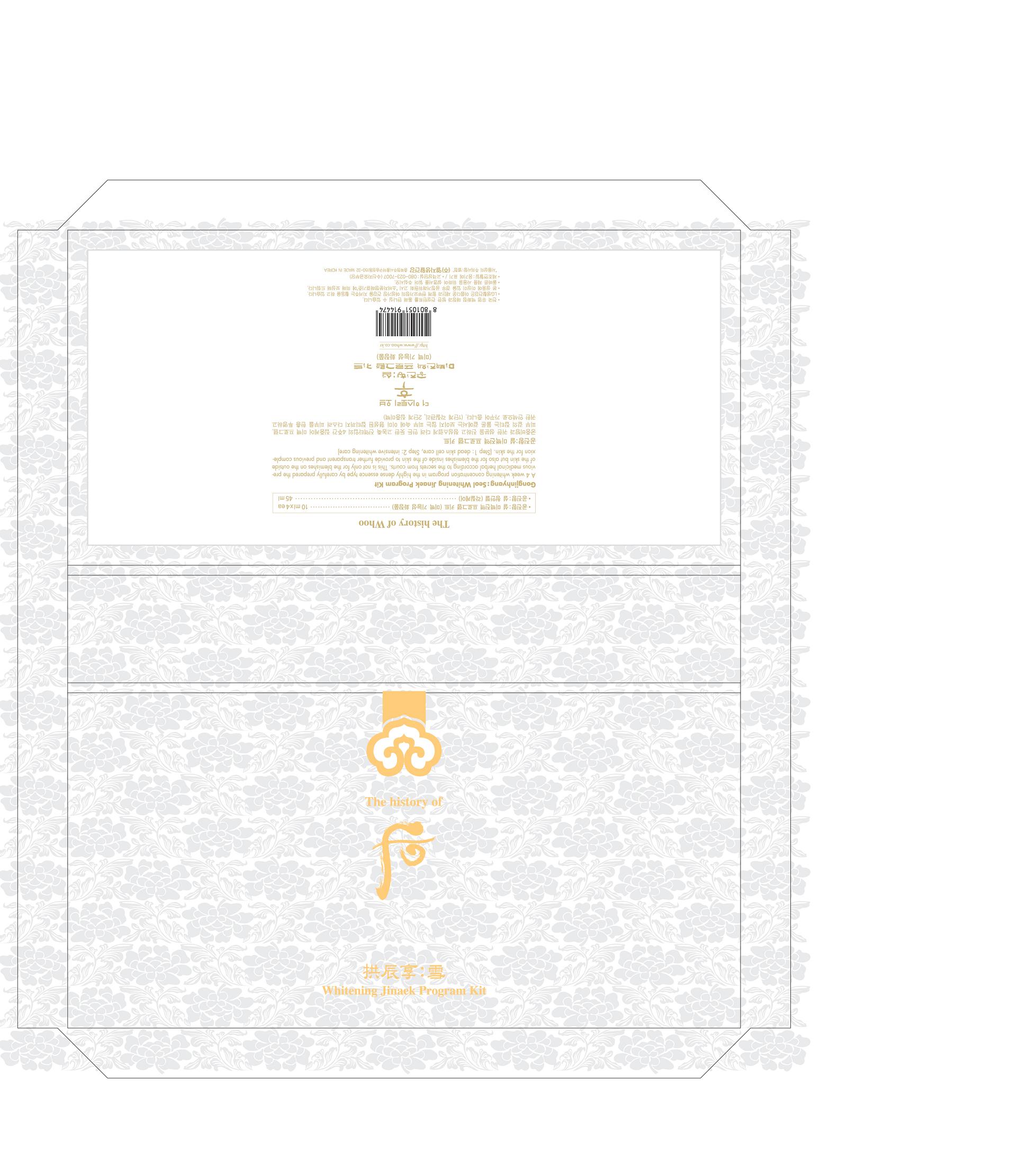 DRUG LABEL: WHOO GONGJINHYANG SEOL WHITENING JINAEK PROGRAM KIT
NDC: 53208-428 | Form: CREAM
Manufacturer: LG Household and Healthcare, Inc.
Category: otc | Type: HUMAN OTC DRUG LABEL
Date: 20100503

ACTIVE INGREDIENTS: TITANIUM DIOXIDE 0.5 mL/100 mL
INACTIVE INGREDIENTS: WATER; CAPRYLIC/CAPRIC MONO/DIGLYCERIDES; CYCLOMETHICONE 5; DIPROPYLENE GLYCOL; DIMETHICONE; 2-ETHYLHEXANOIC ACID; SQUALANE; PANTHENOL; POLYOXYL 40 HYDROGENATED CASTOR OIL; PANTHENOL; MORUS ALBA ROOT BARK; FILIPENDULA ULMARIA FLOWER; GLYCYRRHIZINATE DIPOTASSIUM; DIPROPYLENE GLYCOL; N-ACETYL-TYROSINE; TROLAMINE; EDETATE TRISODIUM; DIOSMETIN

WHOO GONGJINHYANG SEOL WHITENING JINAEK PROGRAM KIT

DRUG FACTS

TITANIUM DIOXIDE 0.5g/100g

WARNINGS AND PRECAUTIONS

For external use only

Keep out of reach of children. Is swallowed, get medical help or contact a Poison Control Center right away.

WHEN USING

Keep out of eyes. Rinse with water to remove.

Stop use if a rash or irritation develops and lasts.